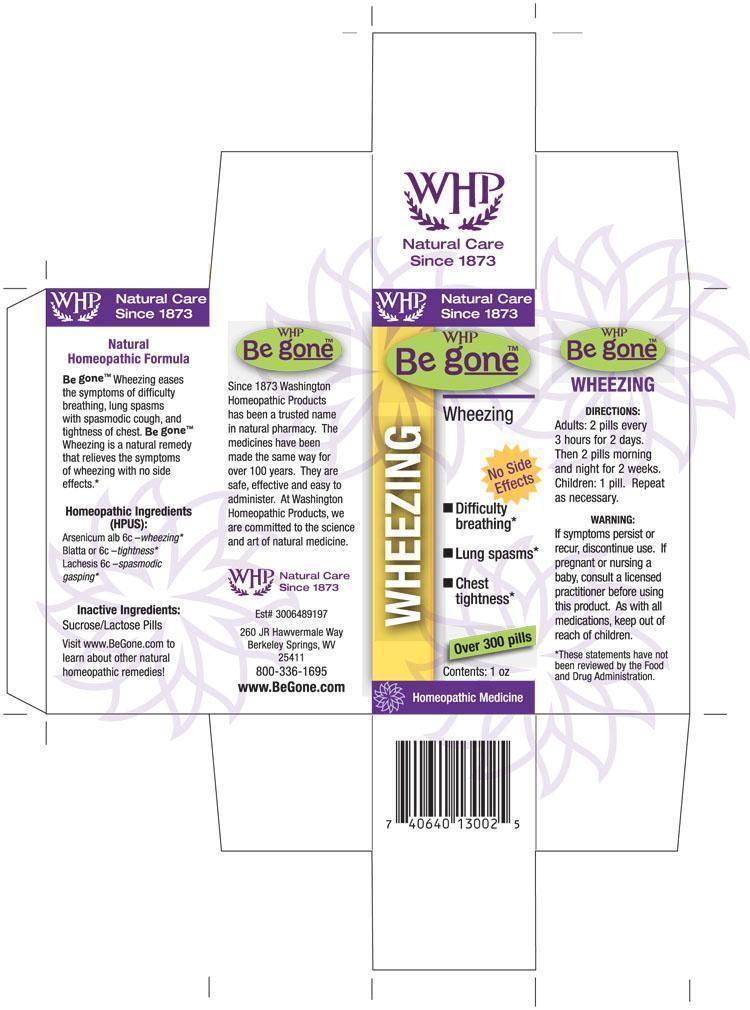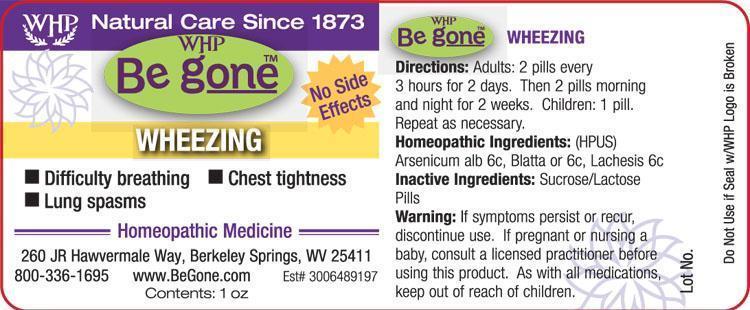 DRUG LABEL: WHP Be gone Wheezing
NDC: 68428-744 | Form: PELLET
Manufacturer: Washington Homeopathic Products
Category: homeopathic | Type: HUMAN OTC DRUG LABEL
Date: 20130920

ACTIVE INGREDIENTS: ARSENIC TRIOXIDE 6 [hp_C]/1 1; BLATTA ORIENTALIS 6 [hp_C]/1 1; LACHESIS MUTA VENOM 6 [hp_C]/1 1
INACTIVE INGREDIENTS: SUCROSE; LACTOSE

DRUG FACTS

ACTIVE INGREDIENTS

ARSENIC TRIOXIDE 6C

BLATTA ORIENTALIS 6C

LACHESIS MUTA VENOM 6C

USES

Eases the symptoms of difficulty breathing, lung spasms with spasmodic cough, and tightness of chest.

KEEP OUT OF REACH OF CHILDREN

As with all medication, keep out of reach of children.

INDICATIONS

ARSENIC TRIOXIDE wheezing

BLATTA ORIENTALIS tightness

LACHESIS MUTA VENOM spasmodic gasping

STOP USE AND ASK DOCTOR

If symptoms persist or recur, discontinue use. If pregnant or nursing a baby, consult a licensed practitioner before using this product.

DIRECTIONS

Adults 2 pills every 3 hours for 2 days. Then 2 pills morning and night for 2 weeks.

Children: 1 pills. Repeat as necessary.

INACTIVE INGREDIENTS

Sucrose/Lactose

PRINCIPAL DISPLAY PANEL

WHP Be goneTM Wheezing label

WHP Be goneTM Wheezing box